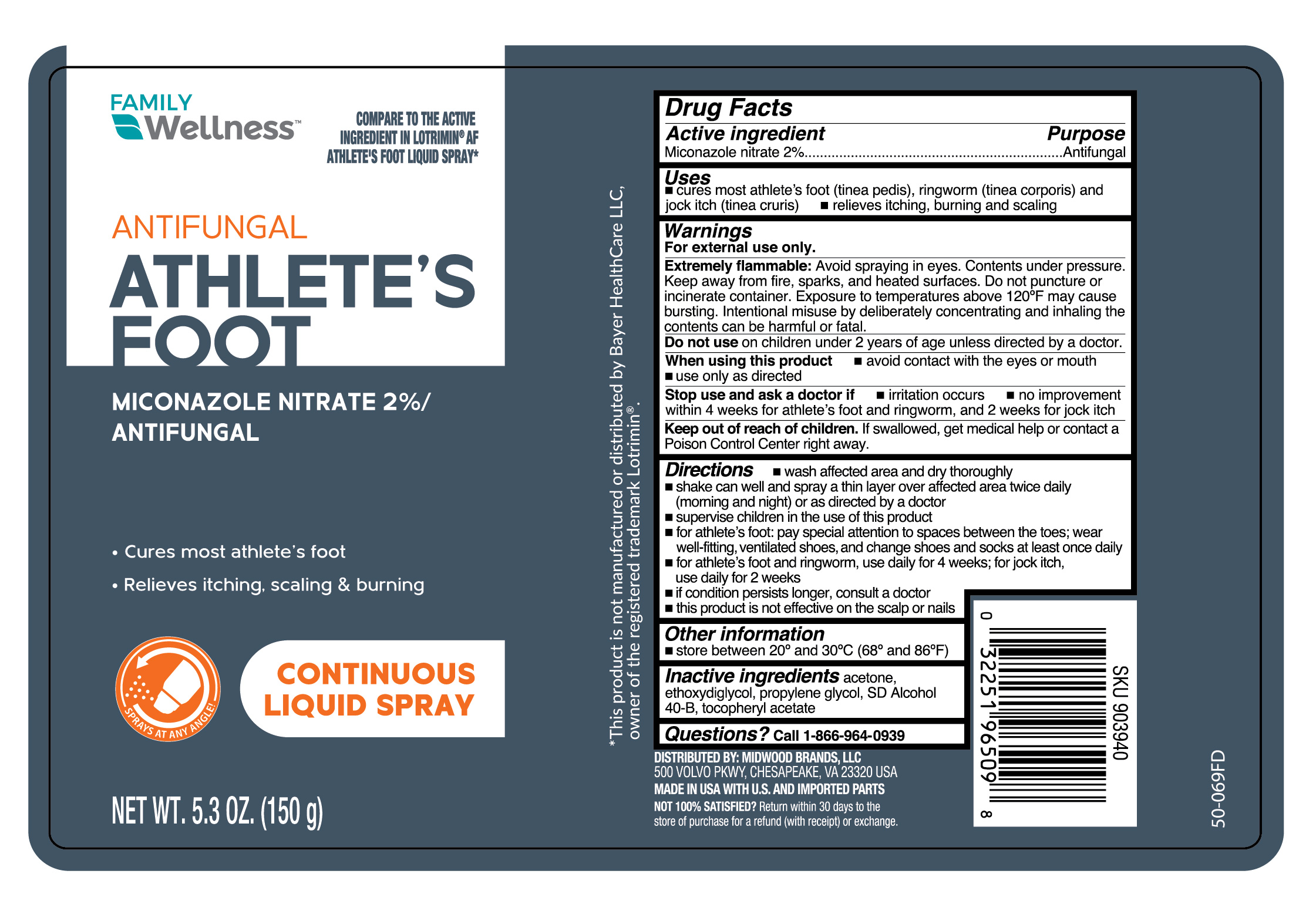 DRUG LABEL: Antifungal Liquid Continuous
NDC: 55319-539 | Form: AEROSOL, SPRAY
Manufacturer: Family Dollar Services, Inc
Category: otc | Type: HUMAN OTC DRUG LABEL
Date: 20251030

ACTIVE INGREDIENTS: MICONAZOLE NITRATE 20 mg/1 g
INACTIVE INGREDIENTS: ACETONE; DIETHYLENE GLYCOL MONOETHYL ETHER; PROPYLENE GLYCOL; ALCOHOL; .ALPHA.-TOCOPHEROL ACETATE

Family Wellness Athlete's Foot Continuous Liquid Spray

Active ingredient

Miconazole nitrate 2%

Purpose

Antifungal

Uses

- cures most athlete's foot (tinea pedis), ringworm (tinea corporis) and jock itch (tinea cruris)
- relieves itching, burning and scaling

Warnings

For external use only.

Extremely flammable:

Avoid spraying in eyes. Contents under pressure. Keep away from fire, sparks, and heated surfaces. Do not puncture or incinerate container. Exposure to temperatures above 120°F may cause bursting. Intentional misuse by deliberately concentrating and inhaling the contents can be harmful or fatal.

When using this product

- avoid contact with the eyes or mouth
- use only as directed

Stop use and ask a doctor if

- irritation occurs
- no improvement within 4 weeks for athlete's foot and ringworm, and 2 weeks for jock itch

Keep out of reach of children.

If swallowed, get medical help or contact a Poison Control Center right away.

Directions

- wash affected area and dry thoroughly
- shake can well and spray a thin layer over affected area twice daily (morning and night) or as directed by a doctor
- supervise children in the use of this product
- for athlete's foot: pay special attention to spaces between the toes; wear well-fitting, ventilated shoes, and change shoes and socks at least once daily
- for athlete's foot and ringworm, use daily for 4 weeks; for jock itch, use daily for 2 weeks
- if condition persists longer, consult a doctor
- this product is not effective on the scalp or nails

Other information

store between 20º and 30ºC (68ºF and 86ºF)

Inactive ingredients

acetone, ethoxydiglycol, propylene glycol, SD alcohol 40-B, tocopheryl acetate

Questions?

Call 1-866-964-0939

Principal Display Panel

FAMILY

Wellness

ANTIFUNGAL

ATHLETE'S

FOOT

MICONAZOLE NITRATE 2%/

ANTIFUNGAL

Cures most athlete's foot

Relieves itching, scaling & burning

CONTINUOUS

LIQUID SPRAY

NET WT. 5.3 OZ. (150 g)